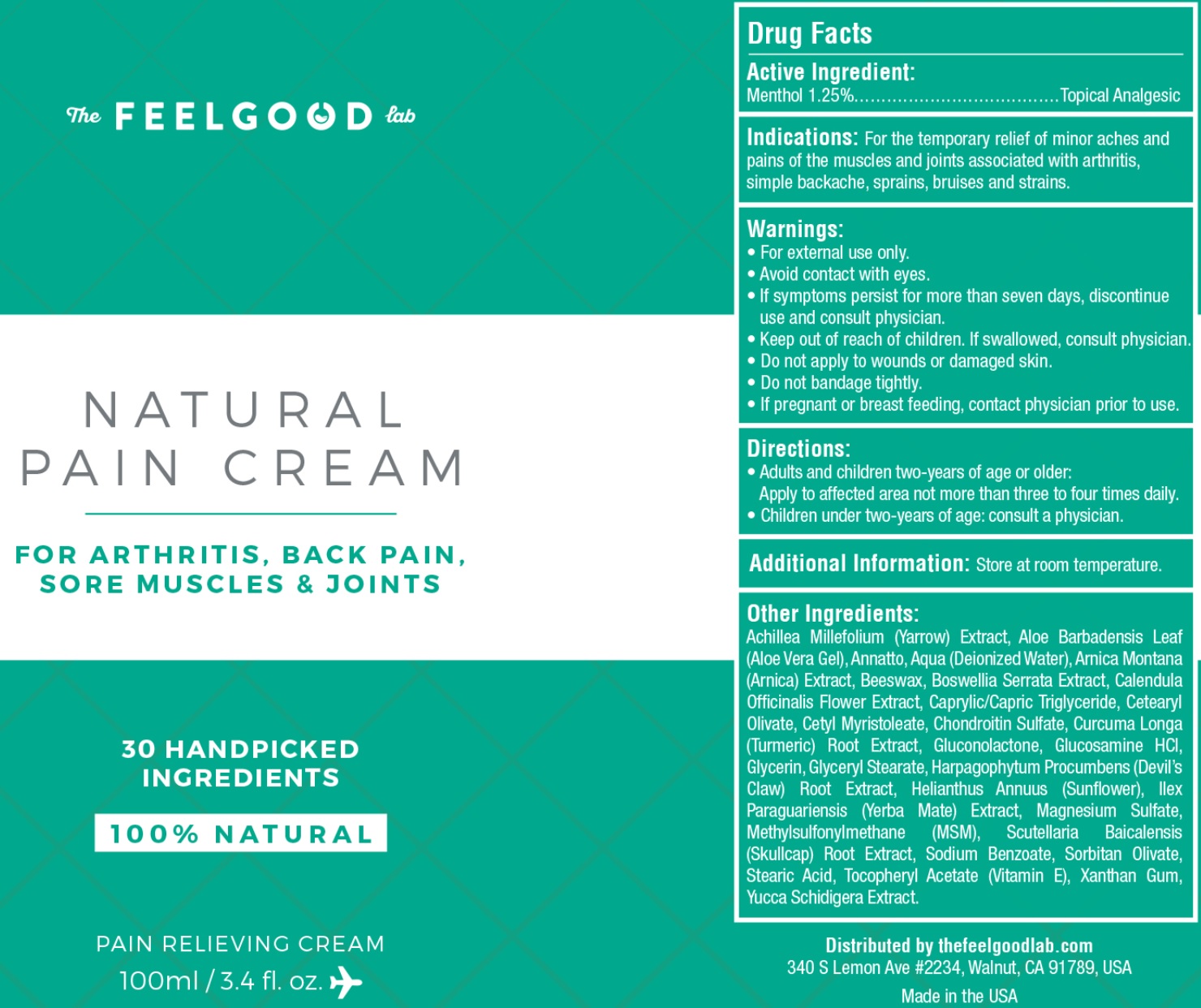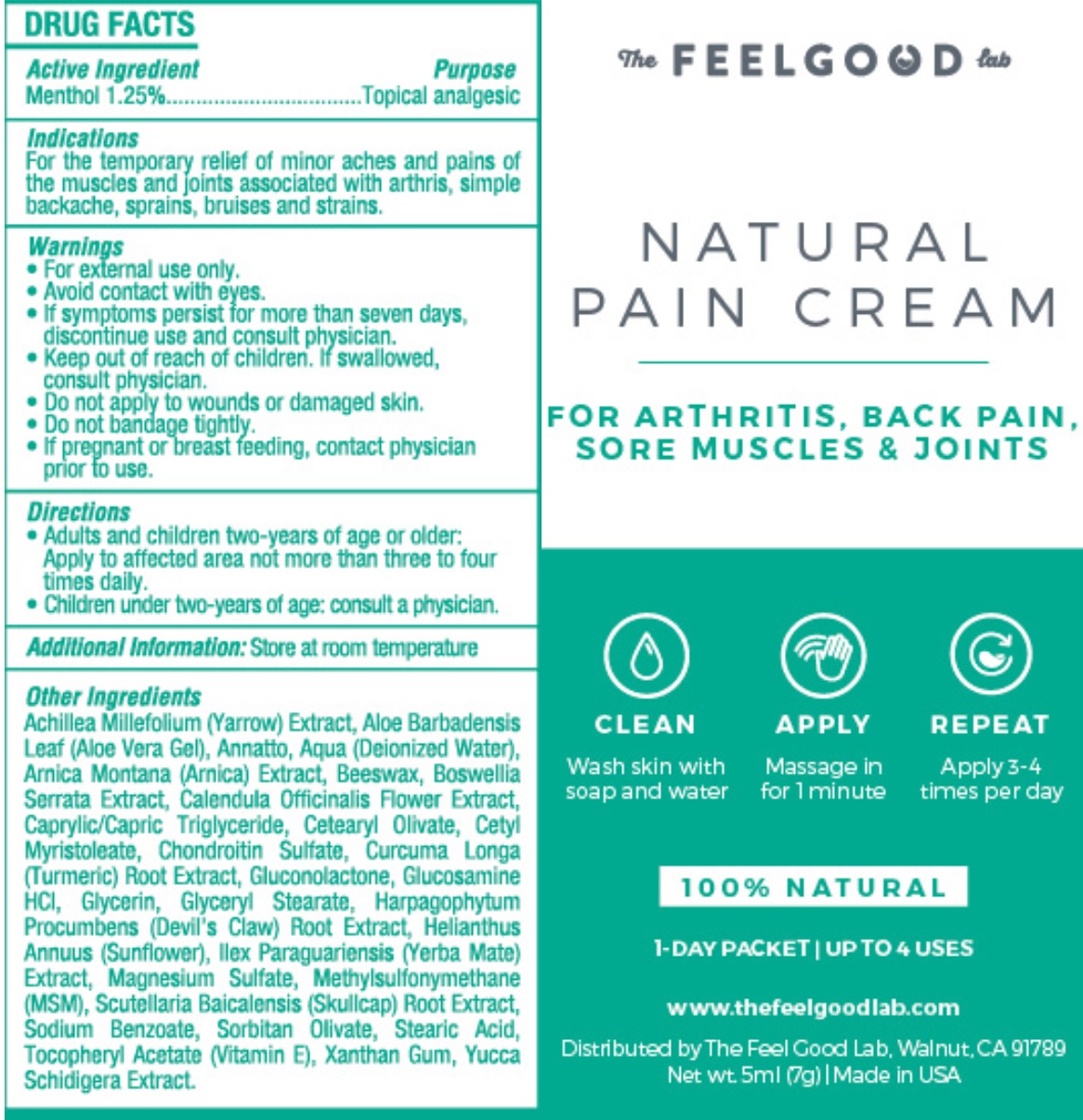 DRUG LABEL: FEEL GOOD LABS NATURAL PAIN
NDC: 70554-260 | Form: LOTION
Manufacturer: The Feel Good Lab
Category: otc | Type: HUMAN OTC DRUG LABEL
Date: 20231105

ACTIVE INGREDIENTS: MENTHOL 12.5 mg/1 mL
INACTIVE INGREDIENTS: ANNATTO; WATER; ARNICA MONTANA; YELLOW WAX; MEDIUM-CHAIN TRIGLYCERIDES; CETEARYL OLIVATE; CETYL MYRISTOLEATE; TURMERIC; GLUCONOLACTONE; GLUCOSAMINE HYDROCHLORIDE; GLYCERIN; GLYCERYL MONOSTEARATE; HARPAGOPHYTUM PROCUMBENS ROOT; ILEX PARAGUARIENSIS LEAF; MAGNESIUM SULFATE, UNSPECIFIED FORM; DIMETHYL SULFONE; SCUTELLARIA BAICALENSIS ROOT; SODIUM BENZOATE; SORBITAN OLIVATE; STEARIC ACID; XANTHAN GUM

FEEL GOOD LABS NATURAL PAIN CREAM

Active Ingredient:

Menthol 1.25%

PURPOSE

Topical Analgesic

Indications:

For the temporary relief of minor aches and pains of the muscles and joints associated with arthritis, simple backache, sprains, bruises and strains.

Warnings:

- For external use only.
- Avoid contact with eyes.
- If symptoms persist for more than seven days, discontinue use and consult physician.

Keep out of reach of children.

- If swallowed, consult physician.

Do not apply

- to wounds or damaged skin.
- Do not bandage tightly.

If pregnant or breast feeding,

contact physician prior to use.

Directions:

- Adults and children two-years of age or older: Apply to affected area not more than three to four times daily.
- Children under two-years of age: consult a physician.

Additional Information:

Store at room temperature.

Other Ingredients:

Achillea Millefolium (Yarrow) Extract, Aloe Barbadensis Leaf (Aloe Vera Gel), Annatto, Aqua (Deionized Water), Arnica Montana (Arnica) Extract, Beeswax, Boswellia Serrata Extract, Calendula Officinalis Flower Extract, Caprylic/Capric Triglyceride, Cetearyl Olivate, Cetyl Myristoleate, Chondroitin Sulfate, Curcuma Longa (Turmeric) Root Extract, Gluconolactone, Glucosamine HCL, Glycerin, Glyceryl Stearate, Harpagophytum Procumbens (Devil's Claw) Root Extract, Helianthus Annuus (Sunflower), Ilex Paraguariensis (Yerba Mate) Extract, Magnesium Sulfate, Methylsulfonylmethane (MSM), Scutellaria Baicalensis (Skullcap) Root Extract, Sodium Benzoate, Sorbitan Olivate, Stearic Acid, Tocopheryl Acetate (Vitamin E), Xanthan Gum, Yucca Schidigera Extract.